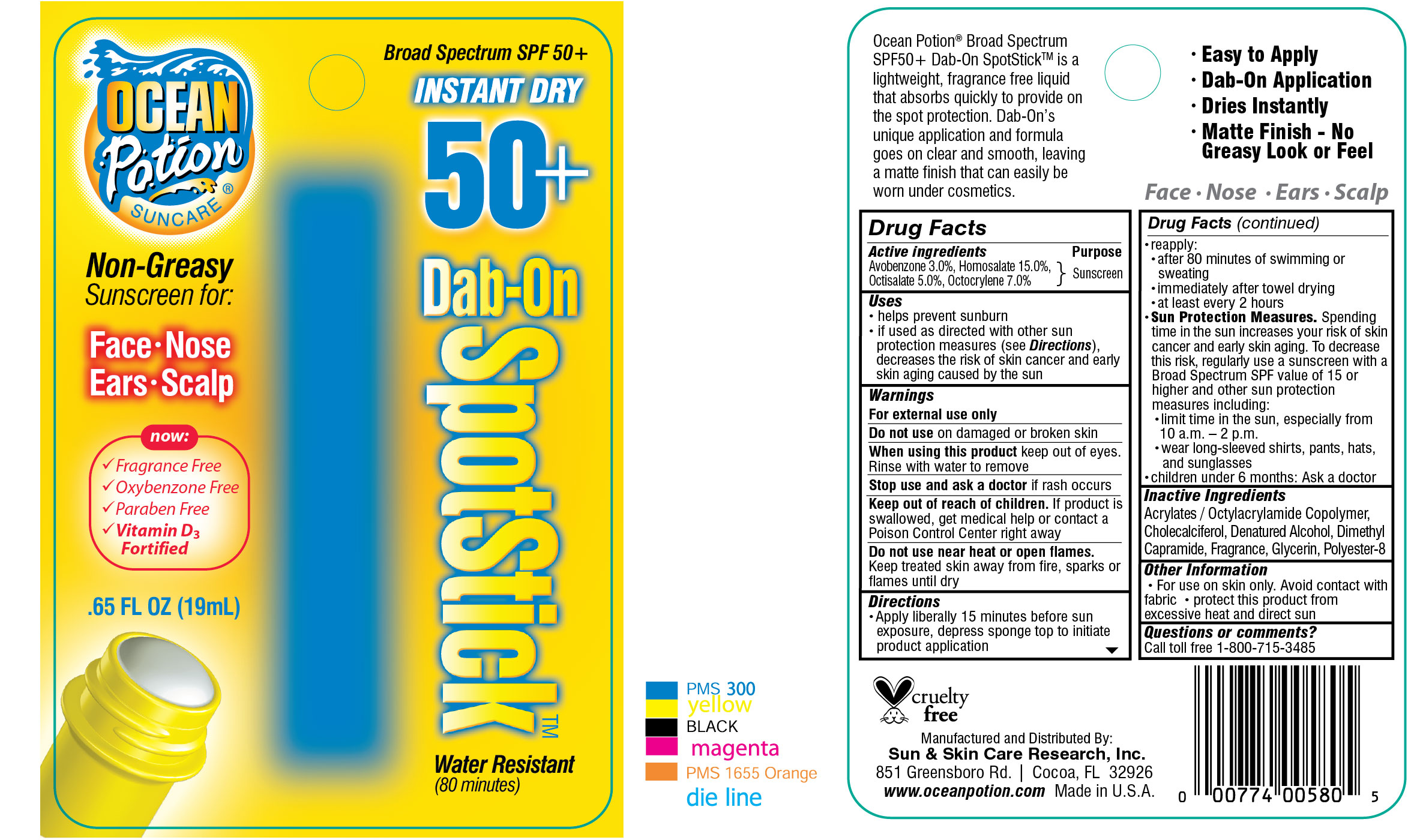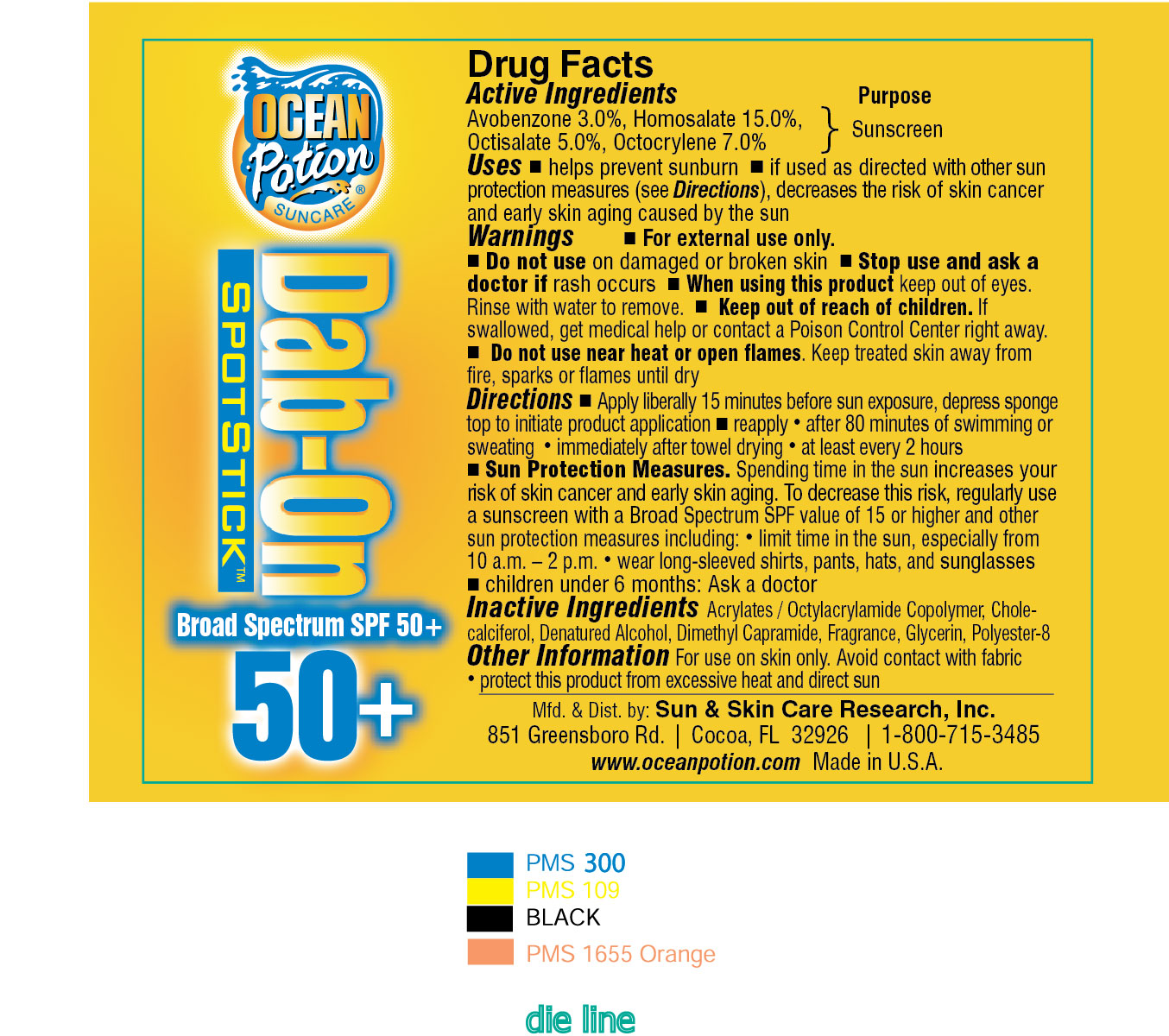 DRUG LABEL: Ocean Potion Instant Dry 50 Dab-On Spotstick 
NDC: 62802-580 | Form: LIQUID
Manufacturer: Sun & Skin Care Research, LLC
Category: otc | Type: HUMAN OTC DRUG LABEL
Date: 20120518

ACTIVE INGREDIENTS: HOMOSALATE 15 mL/100 mL; OCTISALATE 5 mL/100 mL; OCTOCRYLENE 7 mL/100 mL; AVOBENZONE 3 mL/100 mL
INACTIVE INGREDIENTS: ALCOHOL; CHOLECALCIFEROL; DIMETHYL CAPRAMIDE; GLYCERIN; POLYESTER-8 (1400 MW, CYANODIPHENYLPROPENOYL CAPPED)

Drug Facts

Active Ingredients

Homosalate: 15%
Octisalate: 5%
Octocrylene: 7%
Avobenzone: 3%

Purpose

Sunscreen

Uses

- helps prevent sunburn
- If used as directed with other skin protection measures (see Directions), decreases the risk of skin cancer and early skin aging caused by the sun.

Warnings

For external use only. Do not use on damaged or broken skin. Stop use and ask a doctor if rash occurs. When using this product keep out of eyes. Rinse with water to remove. Keep out of the reach of children. If swallowed, get medical help or contact a Poison Control Center right away. Flammable Do not use near heat or open flames. Keep treated skin away from fire, sparks or flames until dry.

Directions

- Apply liberally 15 minutes before sun exposure, depress sponge top to initiate product application
- reapply after 80 minutes of swimming or sweating and immediately after towel drying
- at least every 2 hours
- Sun Protection Measures. Spending time in the sun increases your risk of skin cancer and early skin aging. To decrease this risk, regularly use a sunscreen with a Broad Spectrum SPF value of 15 or higher and other sun protection measures including limiting time in the sun, especially from 10a.m.-2p.m., wear long-sleeved shirts, pants hats and sunglasses.
- children under 6 months: Ask a doctor

Other Information

- For use on skin only
- Avoid contact with fabric
- Protect this product from excessive heat and direct sun